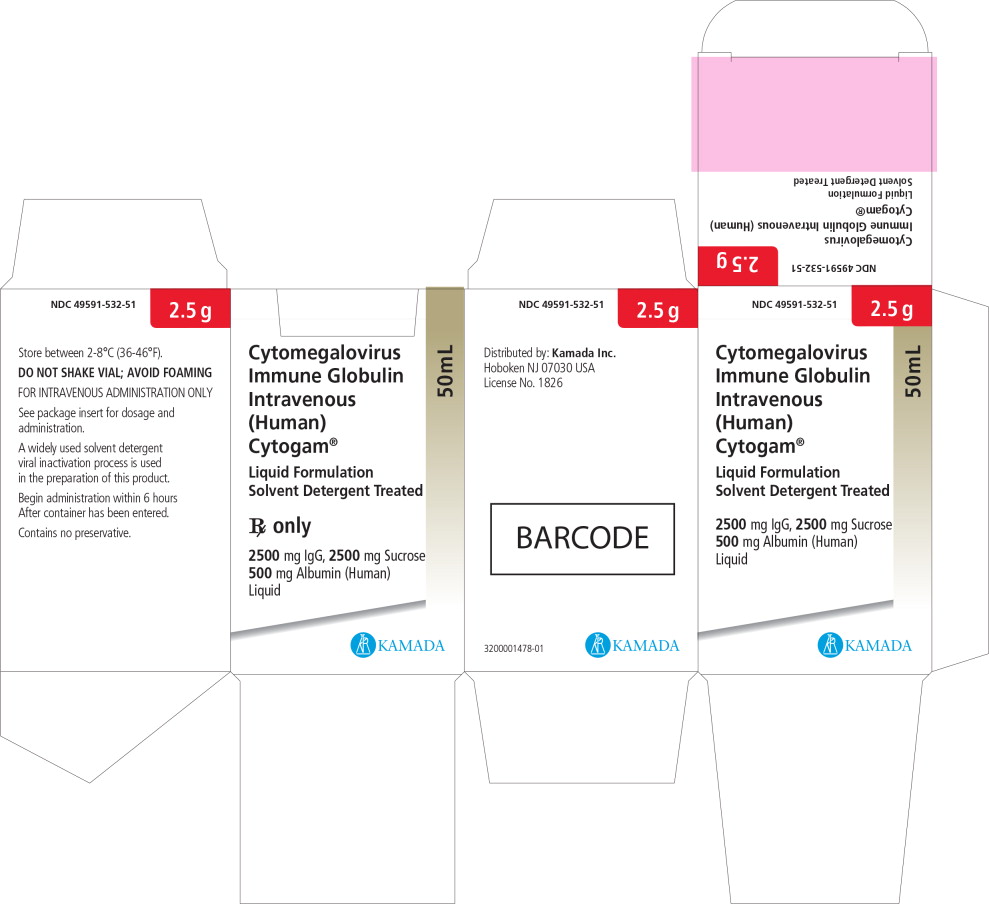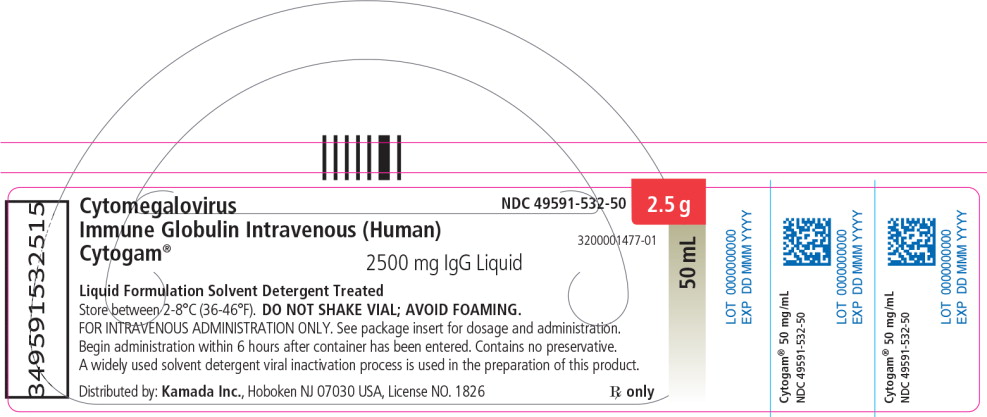 DRUG LABEL: Cytogam
NDC: 49591-532 | Form: LIQUID
Manufacturer: Kamada Ltd.
Category: other | Type: PLASMA DERIVATIVE
Date: 20230228

ACTIVE INGREDIENTS: HUMAN CYTOMEGALOVIRUS IMMUNE GLOBULIN 2500 mg/50 mL
INACTIVE INGREDIENTS: Sucrose; Albumin Human

Kamada Ltd.

CytoGam®
Cytomegalovirus Immune Globulin Intravenous (Human)

Liquid Formulation
Solvent Detergent Treated

Rx only

DESCRIPTION

CytoGam®, Cytomegalovirus Immune Globulin Intravenous (Human) (CMV-IGIV), is an immunoglobulin G (IgG) containing a standardized amount of antibody to Cytomegalovirus (CMV). CMV-IGIV is formulated in final vial as a sterile liquid. The globulin is stabilized with 5% sucrose and 1% Albumin (Human). CytoGam® contains no preservative. The purified immunoglobulin is derived from pooled adult human plasma selected for high titers of antibody for Cytomegalovirus (CMV) (1). Source material for fractionation may be obtained from another U.S. licensed manufacturer. Pooled plasma was fractionated by ethanol precipitation of the proteins according to Cohn Methods 6 and 9, modified to yield a product suitable for intravenous administration. A widely utilized solvent-detergent viral inactivation process is also used (2). Certain manufacturing operations may be performed by other firms. Each milliliter contains: 50 ± 10 mg of immunoglobulin, primarily IgG, and trace amounts of IgA and IgM; 50 mg of sucrose; 10 mg of Albumin (Human). The sodium content is 20-30 mEq per liter, i.e., 0.4-0.6 mEq per 20 mL or 1.0-1.5 mEq per 50 mL. The solution should appear colorless and translucent.

CLINICAL PHARMACOLOGY

CytoGam® contains IgG antibodies representative of the large number of normal persons who contributed to the plasma pools from which the product was derived. The globulin contains a relatively high concentration of antibodies directed against Cytomegalovirus (CMV). In the case of persons who may be exposed to CMV, CytoGam® can raise the relevant antibodies to levels sufficient to attenuate or reduce the incidence of serious CMV disease.

INDICATIONS AND USAGE

Cytomegalovirus Immune Globulin Intravenous (Human) is indicated for the prophylaxis of cytomegalovirus disease associated with transplantation of kidney, lung, liver, pancreas and heart. In transplants of these organs other than kidney from CMV seropositive donors into seronegative recipients, prophylactic CMV-IGIV should be considered in combination with ganciclovir.

CLINICAL STUDIES

Clinical studies have shown a 50% reduction in primary CMV disease in renal transplant patients given CMV-IGIV (3) and a 56% reduction in serious CMV disease (4) in liver transplant patients given CMV-IGIV. CMV-IGIV prophylaxis was associated with increased survival in liver transplant recipients (5).

In two separate clinical trials, CytoGam® was shown to provide effective prophylaxis in renal transplant recipients at risk for primary CMV disease. In the first randomized trial, (3) the incidence of virologically confirmed CMV-associated syndromes was reduced from 60% in controls (n=35) to 21% in recipients of CMV immune globulin (n=24) (P < 0.01); marked leukopenia was reduced from 37% in controls to 4% in globulin recipients (P < 0.01); and fungal or parasitic superinfections were not seen in globulin recipients but occurred in 20% of controls (P = 0.05). Serious CMV disease was reduced from 46% to 13%. There was a concomitant but not statistically significant reduction in the incidence of CMV pneumonia (17% of controls as compared with 4% of globulin recipients). There was no effect on rates of viral isolation or seroconversion although the rate of viremia was less in CytoGam® recipients. In a subsequent non-randomized trial in renal transplant recipients (n=36) (6), the incidence of virologically confirmed CMV-associated syndrome was reduced to 36% in the globulin recipients in comparison to a 60% incidence in control patients (n=35) in the randomized trial. The rates of serious CMV disease, and concomitant fungal and parasitic superinfection were similar to patients receiving CMV-IGIV in the first trial.

In a randomized, double-blind, placebo-controlled trial in liver transplant recipients (4), the incidence of serious CMV-associated disease was reduced from 26% in the 72 control patients to 12% in the 69 CMV-IGIV recipients (p=0.02); serious CMV-associated disease included CMV disease in 2 or more organs, CMV pneumonia, or CMV-associated invasive fungal infection, the incidence of which was 18% in controls and 7% in CMV-IGIV recipients (p=0.04). In follow-up (5) of the liver transplant patients studied in this randomized controlled trial and a subsequent open-label trial (7), the one year survival of the 72 control patients was 72% versus 86% in the 90 recipients of CMV-IGIV (p=0.03). In the randomized control trial, the reduction in serious CMV-associated disease in CMV seronegative recipients of livers from a CMV seropositive donor (7/19 in the CMV-IGIV group vs. 9/19 in control) was less than in transplants with other donor and recipient serologic status (1/50 in the CMV-IGIV group vs. 10/53 in the control group). This finding was similar to that of Merigan et al. (8) in a study of ganciclovir prophylaxis after heart transplantation. In this study, patients received ganciclovir IV at 5 mg/kg twice a day for the initial 14 days post-transplant, then at 6 mg/kg each day for 5 days per week through day 28.

Recent studies of combined prophylaxis with CMV-IGIV and ganciclovir have shown reductions in the incidence of serious CMV associated disease in CMV seronegative recipients of CMV seropositive organs below that expected from one drug alone (9-12).

Ham et al. (9) used CMV-IGIV with a dosage schedule of 150 mg/kg CMV-IGIV within 72 hours of transplant; 100 mg/kg at two, four, six and eight weeks following liver transplant and then 50 mg/kg at 12 and 16 weeks post-transplant in combination with ganciclovir (10 mg/kg/day for 14 days). The incidence of CMV disease was reduced from an expected 60- 80% rate to 7% in 15 seronegative recipients of a seropositive organ.

Snydman (10) using the CMV-IGIV dosage schedule listed under DOSAGE AND ADMINISTRATION section in combination with ganciclovir (10 mg/kg/day for 14 days) reduced the incidence of serious CMV disease in D+R- liver transplant recipients receiving placebo or one drug from 16/47 (34%) to 3/41 (7%) in patients receiving both drugs for prophylaxis.

Martin (11) using CMV-IGIV 100 mg/kg every two weeks for six weeks followed by 50 mg/kg every two weeks with a final dose at week 16, in combination with ganciclovir 10 mg/kg/day for 14 days after transplantation, observed severe CMV disease in 1/74 (1%) of CMV seronegative recipients of a kidney from a CMV seropositive donor, in 0/14 (0%) of CMV seronegative recipients of a kidney-pancreas transplant from a CMV seropositive donor and in 1/12 (8%) of CMV seronegative recipients of a liver from a CMV seropositive donor. The incidence of serious CMV disease with combined CMV-IGIV and ganciclovir prophylaxis was lower than previous experience with single drug prophylaxis.

Valantine and Luikart (12) compared prophylaxis with CMV-IGIV (biweekly for three months) in combination with ganciclovir prophylaxis (IV at 5 mg/kg twice a day for the initial 14 days post-transplant, then at 6 mg/kg through day 28) in 16 CMV seronegative recipients of hearts from CMV seropositive donors with 16 matched controls receiving ganciclovir alone. The actuarial incidence of CMV disease was reduced from 55% in the ganciclovir group to 46% in the combined group (p≤ 0.06) and survival was increased from 61% to 94% (p≤ 0.001). In heart- lung or lung transplant patients in whom either the donor or recipient was CMV seropositive, the actuarial incidence of CMV disease in patients receiving ganciclovir alone (n=25) was 85% as compared to 36% of the 33 patients receiving both CMV-IGIV and ganciclovir (p≤ 0.05). Survival was 60% in the ganciclovir group and 80% in patients receiving CMV-IGIV and ganciclovir (p≤ 0.01).

CONTRAINDICATIONS

CytoGam® should not be used in individuals with a history of a prior severe reaction associated with the administration of this or other human immunoglobulin preparations. Persons with selective immunoglobulin A deficiency have the potential for developing antibodies to immunoglobulin A and could have anaphylactic reactions to subsequent administration of blood products that contain immunoglobulin A, including CytoGam®.

WARNINGS

Because CMV-IGIV is made from human blood, it may carry a risk of transmitting infectious agents, e.g., viruses, the variant Creutzfeldt-Jakob disease (vCJD) agent and, theoretically, the Creutzfeldt-Jakob disease (CJD) agent. The risk of transmission of recognized blood-borne viruses is considered to be low because of the viral inactivation and removal properties in the Cohn-Oncley cold ethanol precipitation procedure used for purification of immune globulin products (13-15). Until 1993, cold ethanol manufactured immune globulins licensed in the United States had not been documented to transmit any viral agent. However, during a brief period in late 1993 to early 1994, intravenous immune globulin made by one U.S. manufacturer was associated with transmission of Hepatitis C virus (16). To further guard against possible transmission of blood- borne viruses, including Hepatitis C, CMV-IGIV is treated with a solvent detergent viral inactivation procedure (2) known to inactivate a wide spectrum of lipid enveloped viruses, including HIV-1, HIV-2, Hepatitis B, and Hepatitis C (17). However, because new blood-borne viruses may yet emerge, some of which may not be inactivated by the manufacturing process or by solvent detergent treatment, CMV-IGIV, like any other blood product, should be given only if a benefit is expected.

Immune Globulin Intravenous (Human) products have been reported to be associated with renal dysfunction, acute renal failure, osmotic nephrosis and death (18-25). Patients predisposed to acute renal failure include patients with any degree of pre-existing renal insufficiency, diabetes mellitus, age greater than 65, volume depletion, sepsis, paraproteinemia or patients receiving known nephrotoxic drugs. Especially in such patients, IGIV products should be administered at the minimum concentrations available and the minimum rate of infusion practicable. While these reports of renal dysfunction and acute renal failure have been associated with the use of many IGIV products, those containing sucrose as a stabilizer (and given at daily doses of 350 mg/kg or greater) account for a disproportionate share of the total number (18). CytoGam® contains sucrose as a stabilizer. See PRECAUTIONS and DOSAGE AND ADMINISTRATION sections for important information intended to reduce the risk of acute renal failure.

During administration, the patient's vital signs should be monitored continuously and careful observation made for any symptoms throughout the infusion. Epinephrine should be available for the treatment of an acute anaphylactic reaction (see PRECAUTIONS section).

PRECAUTIONS

General:

CytoGam® does not contain a preservative. The vial should be entered only once for administration purposes and the infusion should begin within 6 hours. The infusion schedule should be adhered to closely (see Infusion section). Do not use if the solution is turbid.

Although systemic allergic reactions are rare (see ADVERSE REACTIONS section), epinephrine and diphenhydramine should be available for treatment of acute allergic symptoms. If hypotension or anaphylaxis occur, the administration of the immunoglobulin should be discontinued immediately and an antidote should be given as noted above.

Renal Function:

Assure that patients are not volume depleted prior to the initiation of IGIV. Periodic monitoring of renal function tests and urine output is particularly important in patients judged to have a potential increased risk for developing acute renal failure. Renal function, including the measurement of blood urea nitrogen (BUN) and serum creatinine should be assessed prior to the initial infusion of CytoGam® and again at appropriate intervals thereafter. If renal function deteriorates, discontinuation of the product should be considered. The recommended rate of CytoGam® infusion for prophylaxis of CMV disease in solid organ transplant patients is 60 mg Ig/kg/hr (see DOSAGE AND ADMINISTRATION).

Aseptic Meningitis Syndrome:

An aseptic meningitis syndrome (AMS) has been reported to occur infrequently in association with Immune Globulin Intravenous (Human) (IGIV) treatment (26-29). The syndrome usually begins within several hours to two days following IGIV treatment. It is characterized by symptoms and signs including severe headache, nuchal rigidity, drowsiness, fever, photophobia, painful eye movements, and nausea and vomiting. Cerebrospinal fluid (CSF) studies are frequently positive with pleocytosis up to several thousand cells per cu.mm., predominantly from the granulocytic series, and elevated protein levels up to several hundred mg/dL. Patients exhibiting such symptoms and signs should receive a thorough neurological examination, including CSF studies, to rule out other causes of meningitis. AMS may occur more frequently in association with high dose (2 g/kg) IGIV treatment. Discontinuation of IGIV treatment has resulted in remission of AMS within several days without sequelae.

Hemolysis:

Immune Globulin Intravenous (Human) (IGIV) products can contain blood group antibodies which may act as hemolysins and induce in vivo coating of red blood cells with immunoglobulin, causing a positive direct antiglobulin reaction and, rarely, hemolysis (30-32). Hemolytic anemia can develop subsequent to IGIV therapy due to enhanced RBC sequestration (33) [See ADVERSE REACTIONS]. IGIV recipients should be monitored for clinical signs and symptoms of hemolysis [See PRECAUTIONS: Laboratory Tests].

Transfusion-Related Acute Lung Injury (TRALI):

There have been reports of noncardiogenic pulmonary edema [Transfusion-Related Acute Lung Injury (TRALI)] in patients administered IGIV (34). TRALI is characterized by severe respiratory distress, pulmonary edema, hypoxemia, normal left ventricular function, and fever and typically occurs within 1-6 hours after transfusion. Patients with TRALI may be managed using oxygen therapy with adequate ventilatory support.

IGIV recipients should be monitored for pulmonary adverse reactions. If TRALI is suspected, appropriate tests should be performed for the presence of anti-neutrophil antibodies in both the product and patient serum [See PRECAUTIONS: Laboratory Tests].

Thrombotic Events:

Thrombotic events have been reported in association with IGIV (35-37) (See ADVERSE REACTIONS). Patients at risk may include those with a history of atherosclerosis, multiple cardiovascular risk factors, advanced age, impaired cardiac output, and/or known or suspected hyperviscosity. The potential risks and benefits of IGIV should be weighed against those of alternative therapies for all patients for whom IGIV administration is being considered. Baseline assessment of blood viscosity should be considered in patients at risk for hyperviscosity, including those with cryoglobulins, fasting chylomicronemia/markedly high triacylglycerols (triglycerides), or monoclonal gammopathies [See PRECAUTIONS: Laboratory Tests].

Laboratory Tests:

If signs and/or symptoms of hemolysis are present after IGIV infusion, appropriate confirmatory laboratory testing should be done [See PRECAUTIONS].

If TRALI is suspected, appropriate tests should be performed for the presence of anti-neutrophil antibodies in both the product and the patient serum [See PRECAUTIONS].

Because of the potentially increased risk of thrombosis, baseline assessment of blood viscosity should be considered in patients at risk for hyperviscosity, including those with cryoglobulins, fasting chylomicronemia/markedly high triacylglycerols (triglycerides), or monoclonal gammopathies [See PRECAUTIONS].

Drug Interactions:

Antibodies present in immune globulin preparations may interfere with the immune response to live virus vaccines such as measles, mumps, and rubella; therefore, vaccination with live virus vaccines should be deferred until approximately three months after administration of CytoGam®. If such vaccinations were given shortly after CytoGam®, a revaccination may be necessary. Admixtures of CytoGam® with other drugs have not been evaluated. It is recommended that CytoGam® be administered separately from other drugs or medications which the patient may be receiving (see DOSAGE AND ADMINISTRATION section).

Pregnancy:

Animal reproduction studies have not been conducted with Cytomegalovirus Immune Globulin Intravenous (Human). It is also not known whether Cytomegalovirus Immune Globulin Intravenous (Human) can cause fetal harm when administered to a pregnant woman or can effect reproduction capacity. Cytomegalovirus Immune Globulin Intravenous (Human) should be given to a pregnant woman only if clearly needed.

Information for Patients:

Patients should be instructed to report all infections directly to their physician and to Kamada at 1(866)916-0077. The risks and benefits of this product should be discussed with the patient. In addition, patients should be instructed to immediately report symptoms of decreased urine output, sudden weight gain, and/or shortness of breath (which may suggest kidney damage) to their physician.

ADVERSE REACTIONS

Minor reactions such as flushing, chills, muscle cramps, back pain, fever, nausea, vomiting, arthralgia, and wheezing were the most frequent adverse reactions observed during the clinical trials of CytoGam®, Cytomegalovirus Immune Globulin Intravenous (Human). The incidence of these reactions during the clinical trials was less than 6.0% of all infusions and such reactions were most often related to infusion rates. A decrease in blood pressure was observed in 1 of 1039 infusions in clinical trials of CytoGam®. If a patient develops a minor side effect, slow the rate immediately or temporarily interrupt the infusion.

Increases in serum creatinine and blood urea nitrogen (BUN) have been observed as soon as one to two days following IGIV infusion. Progression to oliguria or anuria requiring dialysis has been observed. Types of severe renal adverse events that have been seen following IGIV therapy include acute renal failure, acute tubular necrosis, proximal tubular nephropathy and osmotic nephrosis (18-25).

Severe reactions such as angioneurotic edema and anaphylactic shock, although not observed during clinical trials, are a possibility. Clinical anaphylaxis may occur even when the patient is not known to be sensitized to immune globulin products. A reaction may be related to the rate of infusion; therefore, carefully adhere to the infusion rates as outlined under “DOSAGE AND ADMINISTRATION.” If anaphylaxis or drop in blood pressure occurs, discontinue infusion and use antidote such as diphenhydramine and adrenalin.

Postmarketing:

The following adverse reactions have been identified and reported during the post-approval use of IGIV products (38):

Respiratory: Apnea, Acute Respiratory Distress Syndrome (ARDS), Transfusion Associated Lung Injury (TRALI), cyanosis, hypoxemia, pulmonary edema, dyspnea, bronchospasm

Cardiovascular: Cardiac arrest, thromboembolism, vascular collapse, hypotension

Neurological: Coma, loss of consciousness, seizures, tremor

Integumentary: Stevens-Johnson syndrome, epidermolysis, erythema multiforme, bullous dermatitis

Hematologic: Pancytopenia, leukopenia, hemolysis, positive direct antiglobulin (Coombs) test

General/Body as a Whole: Pyrexia, Rigors

Musculoskeletal: Back pain

Gastrointestinal: Hepatic dysfunction, abdominal pain

Because postmarketing reporting of these reactions is voluntary and the at-risk populations are of uncertain size, it is not always possible to reliably estimate the frequency of the reaction or establish a causal relationship to exposure to the product. Such is also the case with literature reports authored independently.

OVERDOSAGE

Although few data are available, clinical experience with other immunoglobulin preparations suggests that the major manifestations would be those related to volume overload.

DOSAGE AND ADMINISTRATION

The maximum recommended total dosage per infusion is 150 mg Ig/kg, administered according to the following schedule:

 |  | Type of Transplant
 |  | Kidney | Liver, Pancreas,
 |  |  | Lung, Heart
 | Within 72 hours of transplant: | 150 mg/kg | 150 mg/kg
 | 2 weeks post transplant: | 100 mg/kg | 150 mg/kg
 | 4 weeks post transplant: | 100 mg/kg | 150 mg/kg
 | 6 weeks post transplant: | 100 mg/kg | 150 mg/kg
 | 8 weeks post transplant: | 100 mg/kg | 150 mg/kg
 | 12 weeks post transplant: | 50 mg/kg | 100 mg/kg
 | 16 weeks post transplant: | 50 mg/kg | 100 mg/kg

Preparation for Administration. Remove the tab portion of the vial cap and clean the rubber stopper with 70% alcohol or equivalent. DO NOT SHAKE VIAL; AVOID FOAMING.

Parenteral drug products should be inspected visually for particulate matter and discoloration prior to administration whenever solution and container permit. Infuse the solution only if it is colorless, free of particulate matter and not turbid.

Infusion. Infusion should begin within 6 hours after entering the vial and should be complete within 12 hours of entering the vial. Vital signs should be taken preinfusion, mid-way and post- infusion as well as before any rate increase. CytoGam® should be administered through an intravenous line using an administration set that contains an in-line filter (pore size 15μ) and a constant infusion pump (i.e., IVAC pump or equivalent). A smaller in-line filter (0.2μ) is also acceptable. Pre-dilution of CytoGam® before infusion is not recommended. CytoGam® should be administered through a separate intravenous line. If this is not possible, CytoGam® may be “piggybacked” into a pre-existing line if that line contains either Sodium Chloride Injection, USP, or one of the following dextrose solutions (with or without NaCl added): 2.5% dextrose in water, 5% dextrose in water, 10% dextrose in water, 20% dextrose in water. If a pre-existing line must be used, the CytoGam® should not be diluted more than 1:2 with any of the above- named solutions. Admixtures of CytoGam® with any other solutions have not been evaluated.

Initial Dose. Administer intravenously at 15 mg Ig per kg body weight per hour. If no adverse reactions occur after 30 minutes, the rate may be increased to 30 mg Ig/kg/hr; if no adverse reactions occur after a subsequent 30 minutes, then the infusion may be increased to 60 mg Ig/kg/hr (volume not to exceed 75 mL/hour). DO NOT EXCEED THIS RATE OF ADMINISTRATION. The patient should be monitored closely during and after each rate change.

Subsequent Doses. Administer at 15 mg Ig/kg/hr for 15 minutes. If no adverse reactions occur, increase to 30 mg Ig/kg/hr for 15 minutes and then increase to a maximum rate of 60 mg Ig/kg/hr (volume not to exceed 75 mL/hour). DO NOT EXCEED THIS RATE OF ADMINISTRATION.

The patient should be monitored closely during each rate change.

CytoGam® should be used with caution in patients with pre-existing renal insufficiency and in patients judged to be at increased risk of developing renal insufficiency (including, but not limited to those with diabetes mellitus, age greater than 65, volume depletion, paraproteinemia, sepsis and patients receiving known nephrotoxic drugs). In these cases especially, it is important to assure that patients are not volume depleted prior to CytoGam® infusion. While most cases of renal insufficiency have occurred in patients receiving total doses of 350 mg Ig/kg or greater, no prospective data are presently available to identify a maximum safe dose, concentration or rate of infusion in patients determined to be at increased risk of acute renal failure. In the absence of prospective data, recommended doses should not be exceeded and the concentration and infusion rate selected should be the minimum practicable.

Potential adverse reactions are: flushing, chills, muscle cramps, back pain, fever, nausea, vomiting, wheezing, drop in blood pressure. Minor adverse reactions have been infusion rate related – if the patient develops a minor side effect (i.e., nausea, back pain, flushing), slow the rate or temporarily interrupt the infusion. If anaphylaxis or drop in blood pressure occurs, discontinue infusion and use antidote such as diphenhydramine and adrenalin.

To prevent the transmission of hepatitis viruses or other infectious agents from one person to another, sterile disposable syringes and needles should be used. The syringes and needles should not be reused.

HOW SUPPLIED

CytoGam®, Cytomegalovirus Immune Globulin Intravenous (Human), is supplied in one single-dose vial (50 mg/mL). The product presentation includes a carton with a package insert and the following component:

NDC | Component
49591-532-51 | CYTOGAM in a single-dose vial [NDC 49591-532-50]

STORAGE

CytoGam® should be stored between 2-8°C (36-46°F) and used within 6 hours after entering the vial.

REFERENCES

1. Snydman DR, McIver J, Leszczynski J, et al. A pilot trial of a novel cytomegalovirus immune globulin in renal transplant recipients. Transplantation 1984;38:553-557.
2. Horowitz B, Wiebe ME, Lippin A, et al. Inactivation of viruses in labile blood derivatives. Transfusion 1985;25:516-522.
3. Snydman DR, Werner BG, Heinze-Lacey BH, et al. Use of cytomegalovirus immune globulin to prevent cytomegalovirus disease in renal transplant recipients. N Engl J Med 1987;317:1049-1054.
4. Snydman DR, Werner BG, Dougherty NN, et al. Cytomegalovirus Immune Globulin prophylaxis in liver transplantation. A randomized, double-blind, placebo-controlled trial. Ann Int Med 1993;119:984-991.
5. Falagas ME, Snydman DR, Ruthazer R, et al. Cytomegalovirus Immune Globulin (CMVIG) prophylaxis is associated with increased survival after orthotopic liver transplantation. Clin Transplant 1997;11:432-437.
6. Snydman DR, Werner BG, Tilney NL, et al. A final analysis of primary cytomegalovirus disease prevention in renal transplant recipients with a cytomegalovirus immune globulin: Comparison of randomized and open-label trials. Transplant Proc 1991;23:1357-1360.
7. Snydman DR, Werner BG, Dougherty NN, et al. A further analysis of the use of Cytomegalovirus Immune Globulin in orthotopic liver transplant patients at risk for primary infection. Transplant Proc 1994;26 Suppl 1:23-27.
8. Merigan TC, Renlund DG, Keay S, et al. A controlled trial of ganciclovir to prevent cytomegalovirus disease after heart transplantation. N Engl J Med 1992;326:1182-1186.
9. Ham JM, Shelden SR, Godkin RR, et al. Cytomegalovirus prophylaxis with ganciclovir, acyclovir and CMV hyperimmune globulin in liver transplant patients receiving OKT3 induction. Transplant Proc 1995;27 (5 Suppl 1):31-33.
10. Snydman DR. Combined CMV-IGIV and ganciclovir prophylaxis in CMV seronegative transplant recipients from CMV seropositive donors. Report on file.
11. Martin M. CMV prophylaxis with combination ganciclovir and CMV hyperimmune globulin followed by high-dose acyclovir in solid organ transplant recipients. Report on file.
12. Valantine H, Luikart H. Impact of CMV hyperimmune globulin on outcome after cardiothoracic transplantation: A comparative study of combined prophylaxis with CMVIG plus ganciclovir vs. ganciclovir alone. Report on file.
13. Bossell, et al. Safety of therapeutic immune globulin preparations with respect to transmission of human T-lymphotropic virus type III / lymphadenopathy-associated virus infection. MMWR 1996;35:231-233.
14. Wells MA, Wittek AE, Epstein JS, et al. Inactivation and partition of human T-cell lymphotropic virus type III, during ethanol fractionation of plasma. Transfusion 1986;26:210-213.
15. McIver J, Grady G. Immunoglobulin preparations. In: Churchill WH, and Kurtz SR, editors. Transfusion Medicine. Boston: Blackwell Scientific Publications; 1988.
16. Schneider L, Geha R. Outbreak of Hepatitis C associated with intravenous immunoglobulin administration – United States, October 1993 - June 1994. MMWR 1994;43:505-509.
17. Edwards CA, Piet MPJ, Chin S, et al. Tri(nButyl) phosphate detergent treatment of licensed therapeutic and experimental blood derivatives. Vox Sang 1987;52:53-59.
18. Cayco AV, Perazella MA, Hayslett JP. Renal insufficiency after intravenous immune globulin therapy: A report of two cases and an analysis of the literature. J Am Soc Nephrol 1997;8:1788-1794.
19. Cantu TG, Hoehn-Saric EW, Burgess KM, Racusen L, Scheel PJ. Acute renal failure associated with immunoglobulin therapy. Am J Kidney Dis 1995;25:228-234.
20. Hansen-Schmidt S, Silomon J, Keller F. Osmotic nephrosis due to high-dose intravenous immunoglobulin therapy containing sucrose (but not with glycine) in a patient with immunoglobulin A nephritis. Am J Kidney Dis 1996;28: 451-453.
21. Tan E, Hajinazarian M, Bay W, Neff J, Mendell JR. Acute renal failure resulting from intravenous immunoglobulin therapy. Arch Neurol 1993;50:137-139.
22. Winward D, Brophy MT. Acute renal failure after administration of intravenous immunoglobulin: Review of the literature and case report. Pharmacotherapy 1995;15:765- 772.
23. Phillips AO. Renal failure and intravenous immunoglobulin [letter; comment]. Clin Nephrol 1992;37:217.
24. Lindberg HA, Wald MH, Barker MH. Renal changes following administration of hypertonic solutions. Arch Intern Med 1939;63:907-918.
25. Rigdon RH, Cardwell ES. Renal lesions following the intravenous injection of a hypertonic solution of sucrose. Arch Intern Med 1942;69:670-690.
26. Sekul E, Culper E, Dalakas M. Aseptic meningitis associated with high-dose intravenous immunoglobulin therapy; Frequency and risk factors. Ann Intern Med 1994;121:259-262.
27. Kato E, Shindo S, Eto Y, et al. Administration of immune globulin associated with aseptic meningitis. JAMA 1988; 259:3269-3270.
28. Casteels Van Daele M, Wijindaele L, Hunnick K, et al. Intravenous immunoglobulin and acute aseptic meningitis. N Engl J Med 1990;323:614-615.
29. Scribner C, Kapit R, Philips E, et al. Aseptic meningitis and intravenous immunoglobulin therapy. Ann Intern Med 1994;121:305-306.
30. Copelan EA, Strohm PL, Kennedy MS, Tutschka PJ. Hemolysis following intravenous immune globulin therapy. Transfusion 1986;26:410-412.
31. Thomas MJ, Misbah SA, Chapel HM, Jones M, Elrington G, Newsom-Davis J. Hemolysis after high-dose intravenous Ig. Blood 1993;15:3789.
32. Reinhart WH, Berchtold PE. Effect of high dose intravenous immunoglobulin therapy on blood rheology. Lancet 1992;339:662-664.
33. Kessary-Shoham H, Levy Y, Shoenfeld Y, Lorber M, Gershon H. In vivo administration of intravenous immunoglobulin (IVIg) can lead to enhanced erythrocyte sequestration. J Autoimmun 1999;13:129-135.
34. Rizk A, Gorson KC, Kenney L, Weinstein R. Transfusion-related acute lung injury after the infusion of IVIG. Transfusion 2001;41:264-268.
35. Dalakas MC. High-dose intravenous immunoglobulin and serum viscosity: risk of precipitant thromboembolic events. Neurology 1994;44:223-226.
36. Woodruff RK, Grigg AP, Firkin FC, Smith IL. Fatal thrombotic events during treatment of autoimmune thrombocytopenia with intravenous immunoglobulin in elderly patients. Lancet 1986;2:217-218.
37. Wolberg AS, Kon RH, Monroe DM, Hoffman M. Coagulation factor XI is a contaminant in intravenous immunoglobulin preparations. Am J Hematol 2000;65:30-34.
38. Pierce LR, Jain N. Risks associated with the use of intravenous immunoglobulin. Trans Med Rev 2003;17:241-251.

To report SUSPECTED ADVERSE REACTIONS, contact Kamada at 1(866)916-0077 or FDA at 1-800-FDA-1088 or www.fda.gov/medwatch.

If you are having a medical emergency, please contact your healthcare provider or seek medical attention immediately.

For additional information concerning Cytomegalovirus Immune Globulin Intravenous (Human) contact:

Kamada Ltd.
1(866)916-0077

Distributed by: Kamada Inc., Hoboken, NJ 07030

U.S. License No. 1826

Revised 09/2022

Principal Display Panel – 50 mL Carton Label

NDC 49591-532-51

2.5 g

Cytomegalovirus
Immune Globulin
Intravenous
(Human)
Cytogam®

Liquid Formulation

Solvent Detergent Treated

2500 mg IgG, 2500 mg Sucrose

500 mg Albumin (Human)
Liquid

50 mL

Principal Display Panel – 50 mL Vial Label

NDC 49591-532-50

Cytomegalovirus
Immune Globulin Intravenous (Human)
Cytogam®

2500 mg IgG Liquid

50 mL